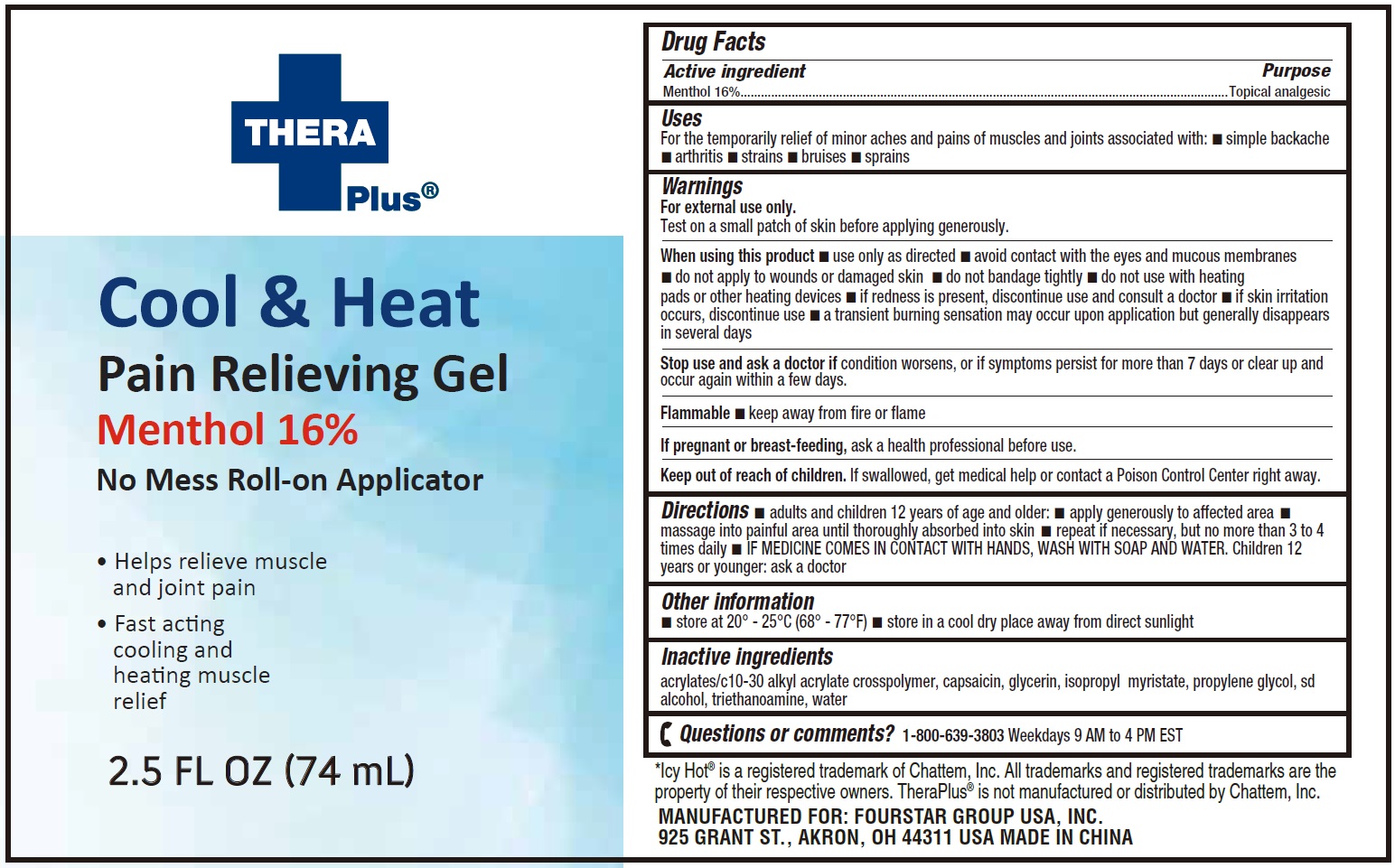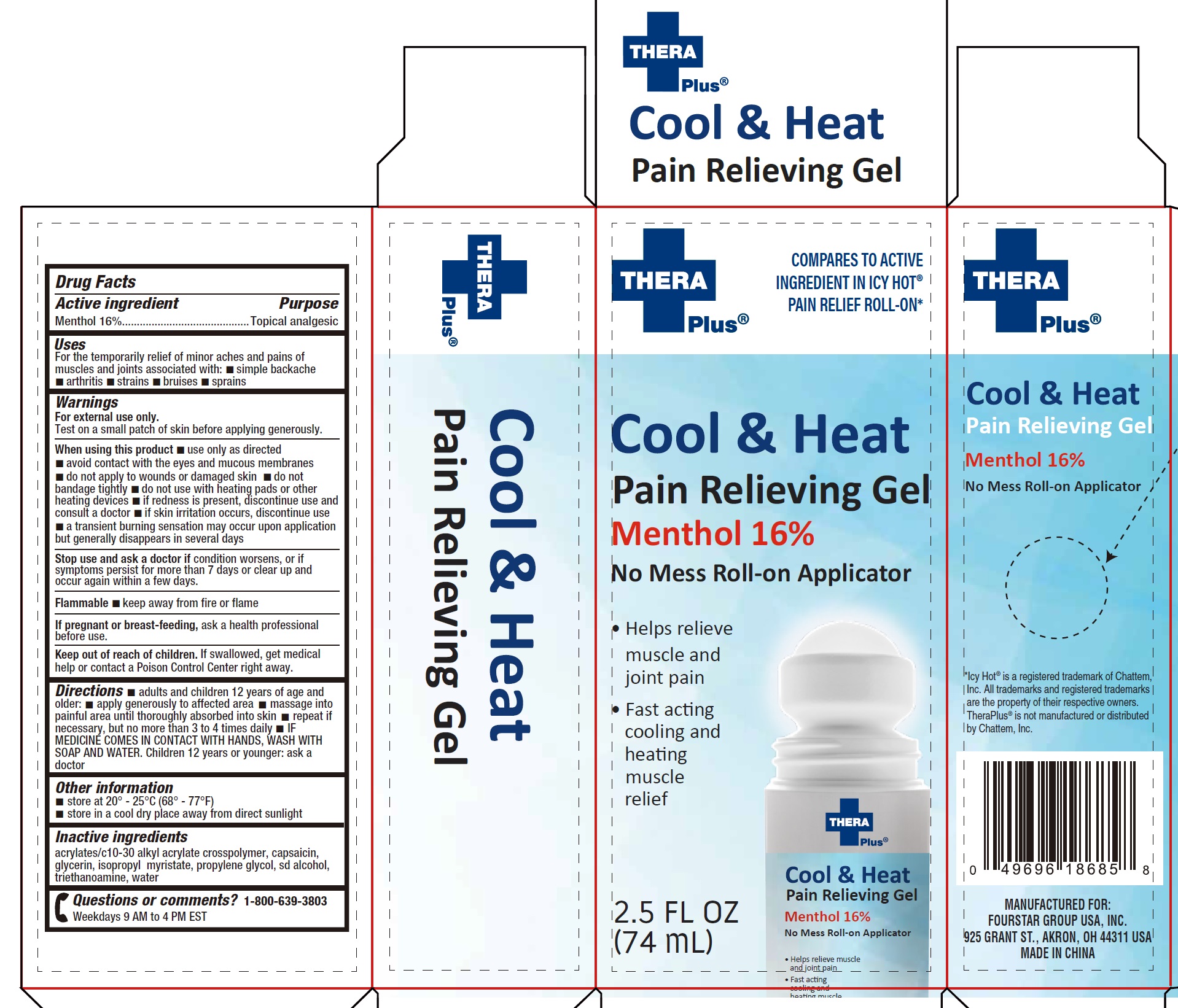 DRUG LABEL: Thera Plus Cool and Heat Pain Relieving Gel Menthol
NDC: 80684-097 | Form: LIQUID
Manufacturer: Fourstar Group USA, Inc.
Category: otc | Type: HUMAN OTC DRUG LABEL
Date: 20231130

ACTIVE INGREDIENTS: MENTHOL 160 mg/1 mL
INACTIVE INGREDIENTS: CAPSAICIN; GLYCERIN; ISOPROPYL MYRISTATE; PROPYLENE GLYCOL; TROLAMINE; WATER

Thera Plus Cool & Heat Pain Relieving Gel Menthol

Active ingredient

Menthol 16%

Purpose

Topical analgesic

Uses

For the temporarily relief of minor aches and pains of muscles and joints associated with: • simple backache • arthritis • strains • bruises • sprains

Warnings

For external use only.

Test on a small patch of skin before applying generously.

Flammable •keep away from fire or flame

When using this product

• use only as directed • avoid contact with the eyes and mucous membranes • do not apply to wounds or damaged skin • do not
bandage tightly • do not use with heating pads or other heating devices • if redness is present, discontinue use and consult a doctor • if skin irritation occurs, discontinue use • a transient burning sensation may occur upon application but generally disappears in several days

Stop use and ask a doctor if

condition worsens, or if symptoms persist for more than 7 days or clear up and occur again within a few days.

If pregnant or breast-feeding,

ask a health professional before use.

Keep out of reach of children.

If swallowed, get medical help or contact a Poison Control Center right away.

Directions

• adults and children 12 years of age and older: • apply generously to affected area • massage into painful area until thoroughly absorbed into skin • repeat if necessary, but no more than 3 to 4 times daily • IF MEDICINE COMES IN CONTACT WITH HANDS, WASH WITH SOAP AND WATER. Children 12 years or younger: ask a doctor

Other information

- store at 20° - 25°C (68° - 77°F)
- store in a cool dry place away from direct sunlight

Inactive ingredients

acrylates/c10-30 alkyl acrylate crosspolymer, capsaicin, glycerin, isopropyl myristate, propylene glycol, sd alcohol, triethanoamine, water

Questions or comments?

1-800-639-3803 Weekdays 9 AM to 4 PM EST